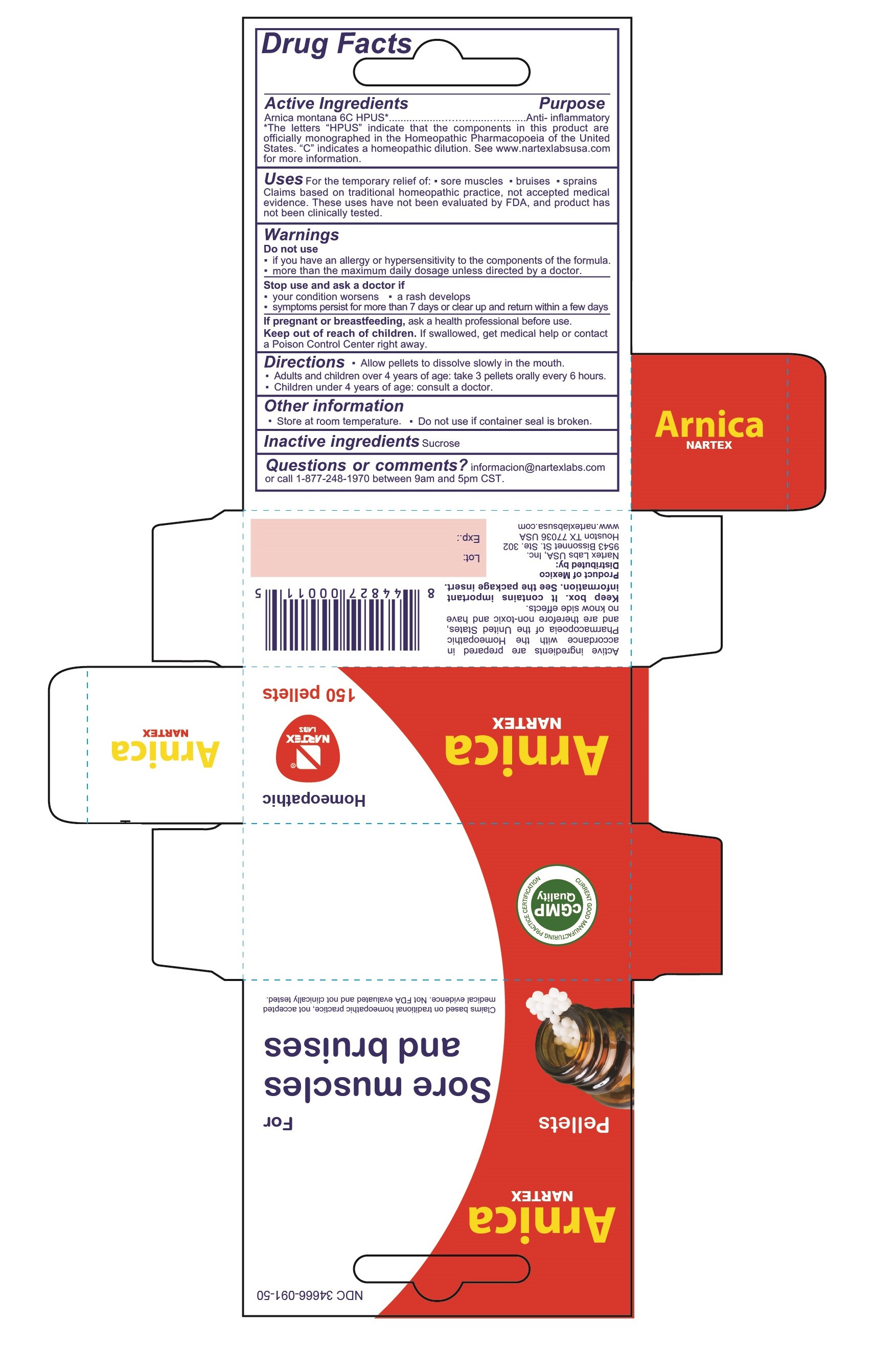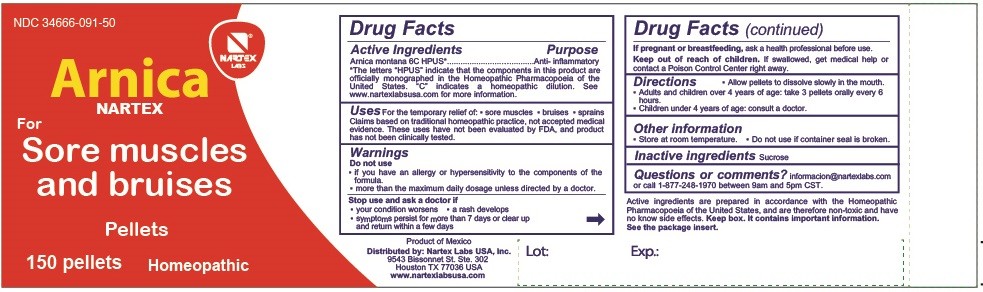 DRUG LABEL: Arnica Montana
NDC: 34666-091 | Form: PELLET
Manufacturer: NARTEX LABORATORIOS HOMEOPATICOS SA DE CV
Category: homeopathic | Type: HUMAN OTC DRUG LABEL
Date: 20250813

ACTIVE INGREDIENTS: ARNICA MONTANA 6 [hp_C]/1 1
INACTIVE INGREDIENTS: SUCROSE

ACTIVE INGREDIENT

Arnica montana......6C HPUS

PURPOSE

Arnica montana.......6C HPUS*......anti-inflammatory

*The letters "HPUS" indicate that the components in this product are officially monographed in the Homeopathic Pharmacopoeia of the United States. "C" indicates a homeopathic dilution. See www.nartexlabsusa.com for more information.

INDICATIONS AND USAGE

For the temporary relief of:

- sore muscles
- bruises
- sprains

Claims based on traditional homeopathic practice, not accepted medical evidence. These uses have not been evaluated by FDA, and product has not been clinically tested.

Do not use

- if you have an allergy or hypersensitivity to the components of the formula.
- more than the maximum daily dosage unless directed by a doctor.

Stop use and ask a doctor if:

- condition worsens
- a rash develops
- symptoms persist for more than 7 days or clear up and return within a few days

PREGNANCY OR BREAST FEEDING

If pregnant or breast feeding, consult a health professional.

Keep out of reach of children.If swallowed, get medical help or contact a Poison Control Center right away.

Directions

- Allow pellets to dissolve slowly in the mouth.
- Adults and children over 4 years of age: take 3 pellets orally every 6 hours.
- Children under 4 years of age: consult a doctor.

STORAGE AND HANDLING

- Store at room temperature.
- Do not use if container seal is broken.

INACTIVE INGREDIENT

Sucrose

Questions or comments? informacion@nartexlabs.comor call 1-877-248-1970 between 9am and 5pm CST

DESCRIPTION

Active ingredients are prepared in accordance with the Homeopathic Pharmacopoeia of the United States, and are therefore non-toxic and have no known side effects.

Keep box. It contains important information. See the package insert.

DESCRIPTION

Distributed by:

Nartex Labs USA, Inc.

9543 Bissonnet St. Ste. 302

Houston TX 77036 USA

www.nartexlabsusa.com

PACKAGE LABEL

NDC 34666-091-50

Arnica

Nartex

Pellets

For Sore muscles and bruises

Claims based on traditional homeopathic practice, not accepted medical evidence. Not FDA evaluated and not clinically tested.

Homeopathic

150 pellets